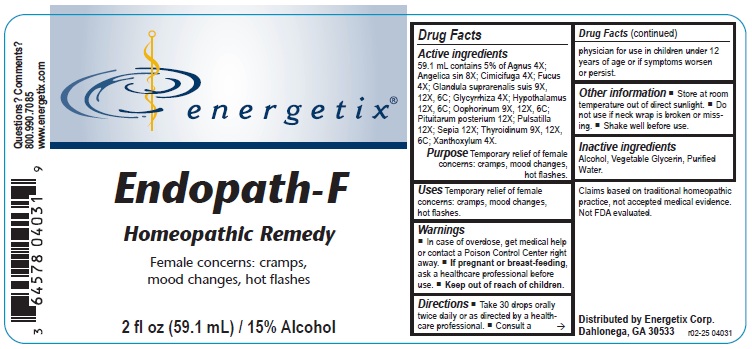 DRUG LABEL: Endopath-F
NDC: 64578-0170 | Form: LIQUID
Manufacturer: Energetix Corporation
Category: homeopathic | Type: HUMAN OTC DRUG LABEL
Date: 20250715

ACTIVE INGREDIENTS: CHASTE TREE FRUIT 4 [hp_X]/59.1 mL; ANGELICA SINENSIS ROOT 8 [hp_X]/59.1 mL; BLACK COHOSH 4 [hp_X]/59.1 mL; FUCUS VESICULOSUS 4 [hp_X]/59.1 mL; SUS SCROFA ADRENAL GLAND 9 [hp_X]/59.1 mL; LICORICE 4 [hp_X]/59.1 mL; BOS TAURUS HYPOTHALAMUS 12 [hp_X]/59.1 mL; SUS SCROFA OVARY 9 [hp_X]/59.1 mL; SUS SCROFA PITUITARY GLAND, POSTERIOR 12 [hp_X]/59.1 mL; PULSATILLA VULGARIS 12 [hp_X]/59.1 mL; SEPIA OFFICINALIS JUICE 12 [hp_X]/59.1 mL; THYROID, UNSPECIFIED 9 [hp_X]/59.1 mL; ZANTHOXYLUM AMERICANUM BARK 4 [hp_X]/59.1 mL
INACTIVE INGREDIENTS: ALCOHOL; WATER; GLYCERIN

Endopath-F

ACTIVE INGREDIENT

Active ingredients 59.1 mL contains 5% Agnus 4X; Angelica sin 8X; Cimicifuga 4X; Fucus 4X; Glandula suprarenalis suis 9X, 12X, 6C; Glycyrrhiza 4X; Hypothalamus 12X, 6C; Oophorinum 9X, 12X, 6C; Pituitarum posterium 12X; Pulsatilla 12X; Sepia 12X; Thyroidinum 9X, 12X, 6C; Xanthoxylum 4X.

Claims based on traditional homeopathic practice, not accepted medical evidence. Not FDA evalualted.

Uses

Temporary relief of female concerns: cramps, mood changes, hot flashes.

Warnings

- In case of overdose, get medical help or contact a Poison Control Center right away.
- If pregnant or breast feeding,ask a health professional before use.
- Keep out of reach of children.

Keep out of reach of children

Directions

- Take 30 drops orally twice daily or as directed by a healthcare professional.
- Consult a physician for use in children under 12 years of age or if symptoms worsen or persist.

Other information

- Store at room temperature out of direct sunlight.
- Do not use if neck wrap is broken or missing.
- Shake well before use.

Inactive ingredients

Alcohol, Vegetable Glycerin, Purified Water.

QUESTIONS

Distributed by

Energetix Corp.

Dahlonega, GA 30533

Questions? Comments?

800.990.7085

www.energetix.com

PACKAGE LABEL

energetix

Endopath-F

Homeopathic Remedy

Female concerns: cramps, mood changes, hot flashes

2 fl oz (59.1mL) / 15% Alcohol

PURPOSE

Purpose Temporary relief of female concerns: cramps, mood changes, hot flashes.